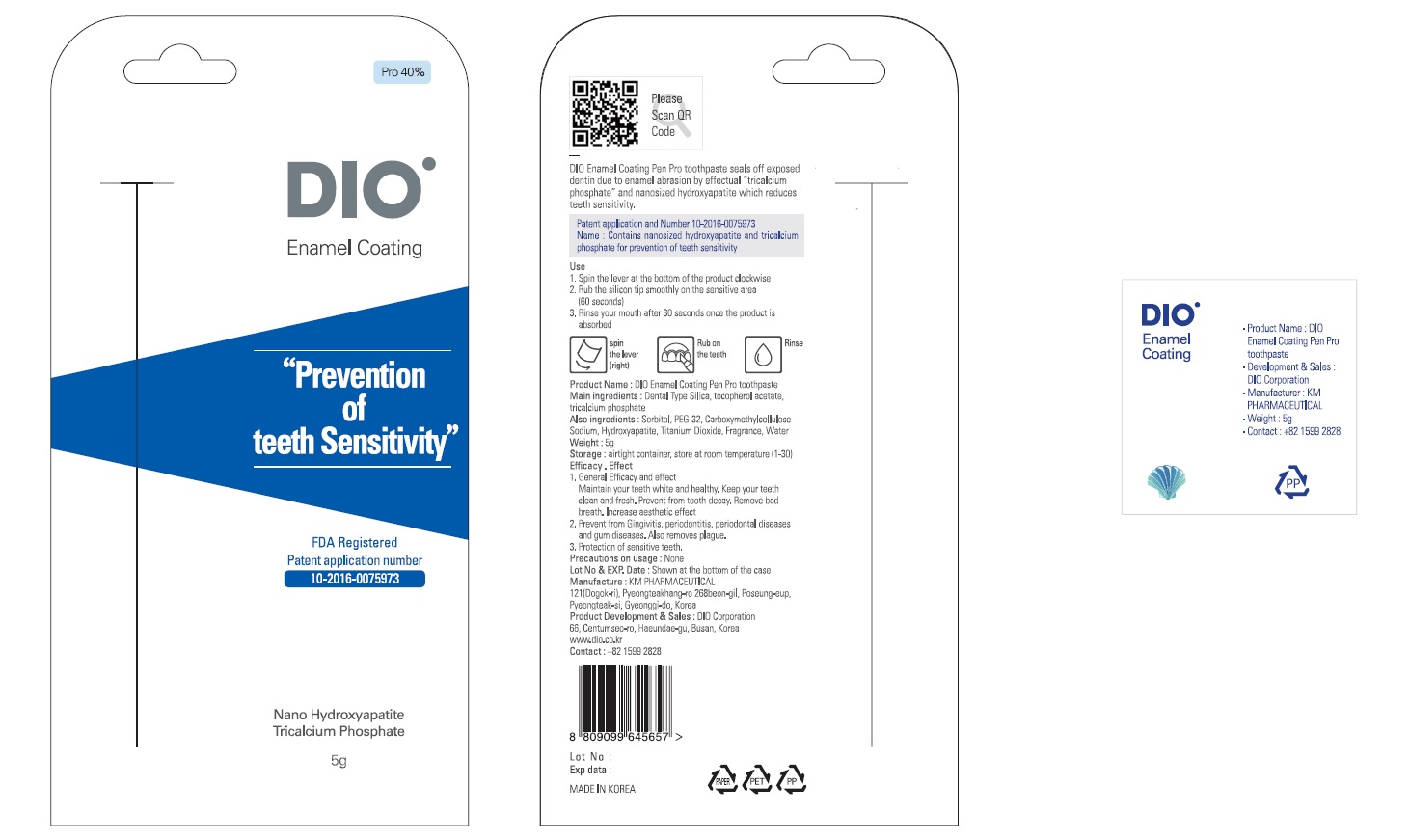 DRUG LABEL: DIO Enamel Coating Pen Pro Tooth
NDC: 75902-6001 | Form: PASTE, DENTIFRICE
Manufacturer: Dio Corporation
Category: otc | Type: HUMAN OTC DRUG LABEL
Date: 20170601

ACTIVE INGREDIENTS: TRICALCIUM PHOSPHATE 20 g/100 g; .ALPHA.-TOCOPHEROL ACETATE 0.2 g/100 g; SILICON DIOXIDE 6 g/100 g
INACTIVE INGREDIENTS: SORBITOL; WATER

ACTIVE INGREDIENT

Tricalcium Phosphate, Dental Type Silica (Silicon Dioxide), Tocopheryl Acetate (.ALPHA.-TOCOPHEROL ACETATE)

PURPOSE

For dental care

Keep out of reach of children

INDICATIONS AND USAGE

1. Spin the lever at the bottom of the product clockwise
2. Rub the silicon tip smoothly on the sensitive area (60 seconds)
3. Rinse your mouth after 30 seconds once the product is absorbed)

WARNINGS

Alright container, store at room temperature (1-30)

INACTIVE INGREDIENT

Sorbitol, water, etc.

DOSAGE AND ADMINISTRATION

For dental use only